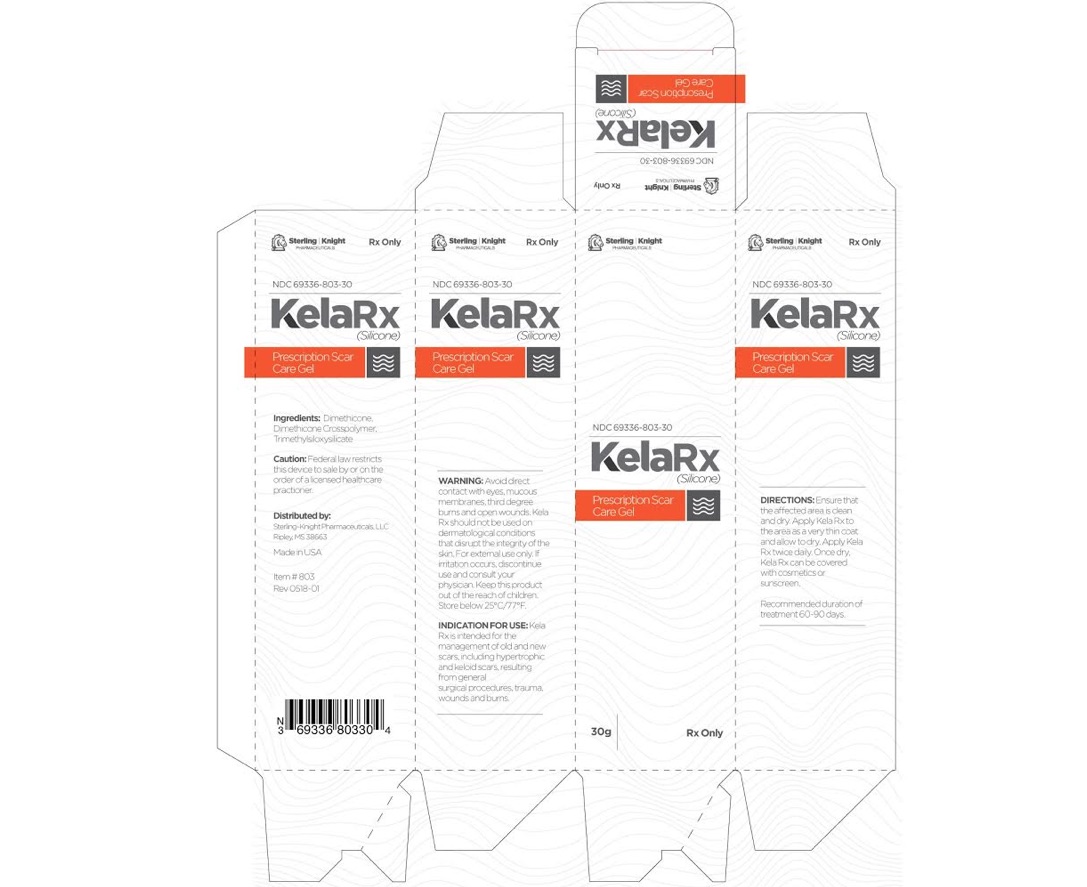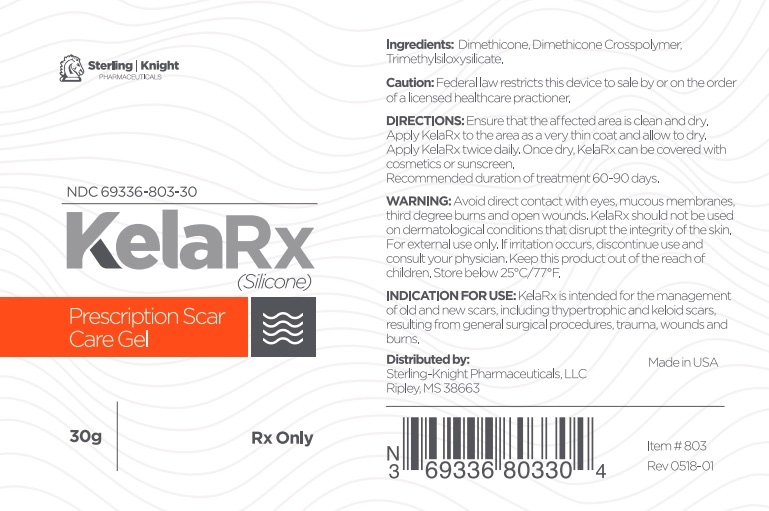 DRUG LABEL: KelaRx
NDC: 69336-803
Manufacturer: Sterling-Knight Pharmaceuticals, LLC
Category: other | Type: MEDICAL DEVICE
Date: 20180921
INACTIVE INGREDIENTS: DIMETHICONE; DIMETHICONE/DIENE DIMETHICONE CROSSPOLYMER; TRIMETHYLSILOXYSILICATE (M/Q 0.6-0.8)

KelaRx
Scar Care Gel

KelaRx™

Scar Care Gel

Prescription Only

KelaRx Scar Care Gel Description

For Old and New Scars

•Reduces redness

•Softens and flattens raised scars

•Relieves itching, discomfort and pain associated with scars

•Helps prevent excessive and abnormal scar formation

•For use as mono-therapy or in combination with other scar therapies, including pressure garments.

KelaRx™ is a self-drying, flexible, gas permeable, waterproof silicone gel that is colorless and odorless. KelaRx™ forms a bond with the stratum corneum (the outer layer of dead skin cells) forming a protective barrier against chemical physical and microbial invasion of the scar site while assisting with hydration.

KelaRx™ is also for use on children or people with sensitive skin. Silicone Gel Sheets are internationally recommended as the first line of treatment in scar management.

Ingredients:

Dimethicone, Dimethicone Crosspolymer, Trimethylsiloxysilicate.

INDICATIONS

KelaRx™ is intended for the management of old and new scars, including hypertrophic and keloid scars, resulting from general surgical procedures, trauma, wounds and burns.

WARNINGS

Avoid direct contact with eyes, mucous membranes, third degree burns and open wounds. KelaRx™ should not be used on dermatological conditions that disrupt the integrity of the skin. For external use only. If irritation occurs, discontinue use and consult your physician. Keep this product out of the reach of children. Store below 25°C/77°F.

PRECAUTIONS

Caution:

Federal law restricts this device to sale by or on the order by a licensed healthcare practitioner.

CALL YOUR DOCTOR ABOUT SIDE EFFECTS.

Call your doctor about side effects. You may report side effects to the FDA at 1-800-FDA-1088.

DOSAGE AND ADMINISTRATION

Ensure that the affected area is clean and dry. Apply KelaRx™to the area as a very thin coat and allow to dry. Apply KelaRx™ twice daily. Once dry, KelaRx™ can be covered with cosmetics or sunscreen. Recommended duration of treatment 60-90 days.

HOW SUPPLIED

KelaRx™ Scar Care Gel is supplied as a white gel in:
30 g tube, NDC 69336-803-30

Distributed By:

Sterling-Knight Pharmaceuticals, LLC
Ripley, MS 38663

Made in USA
Rev 0518-1

PRINCIPAL DISPLAY PANEL

Sterling-Knight Pharmaceuticals, LLC

Ripley, MS 38663
Made in USA
Rev 0518-1

KelaRx™

Scar Care Gel

Prescription Only